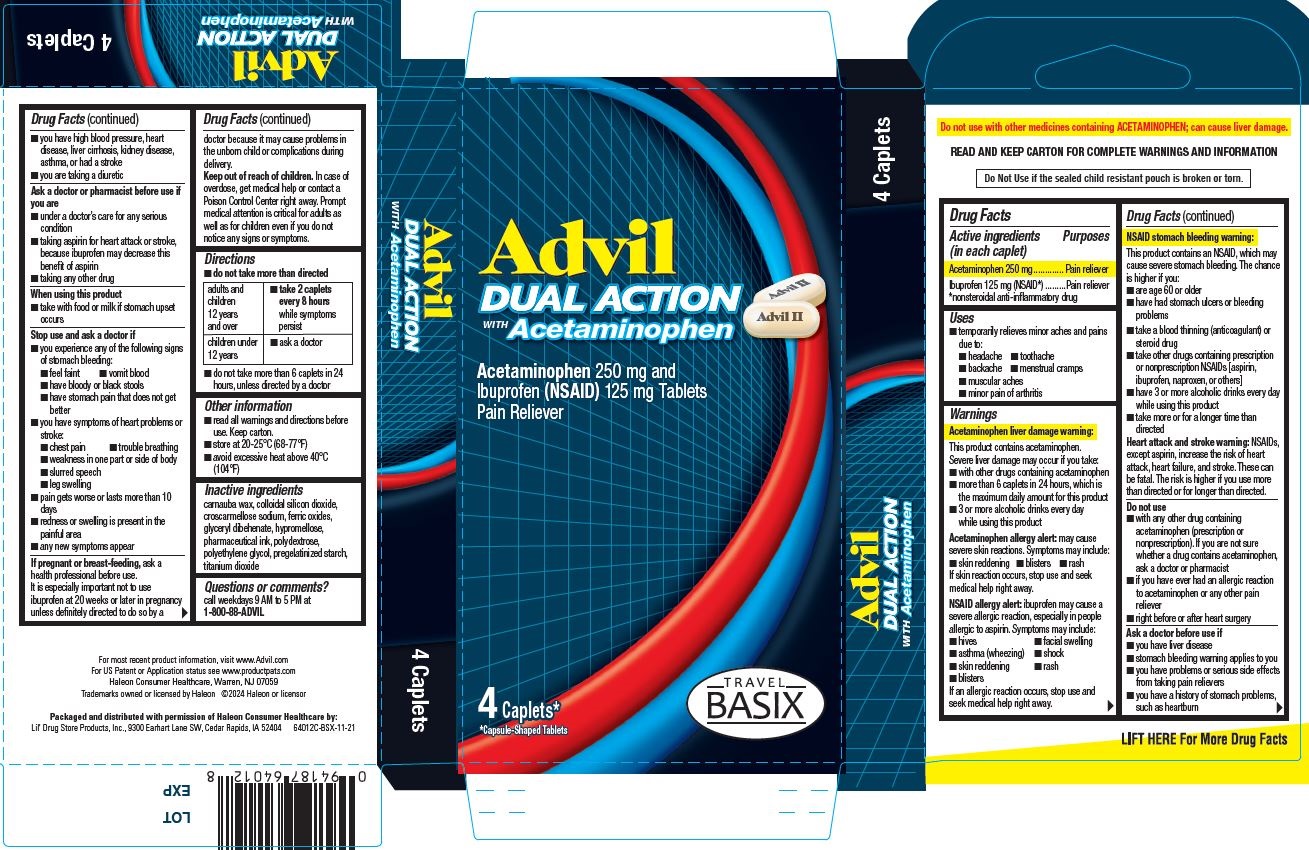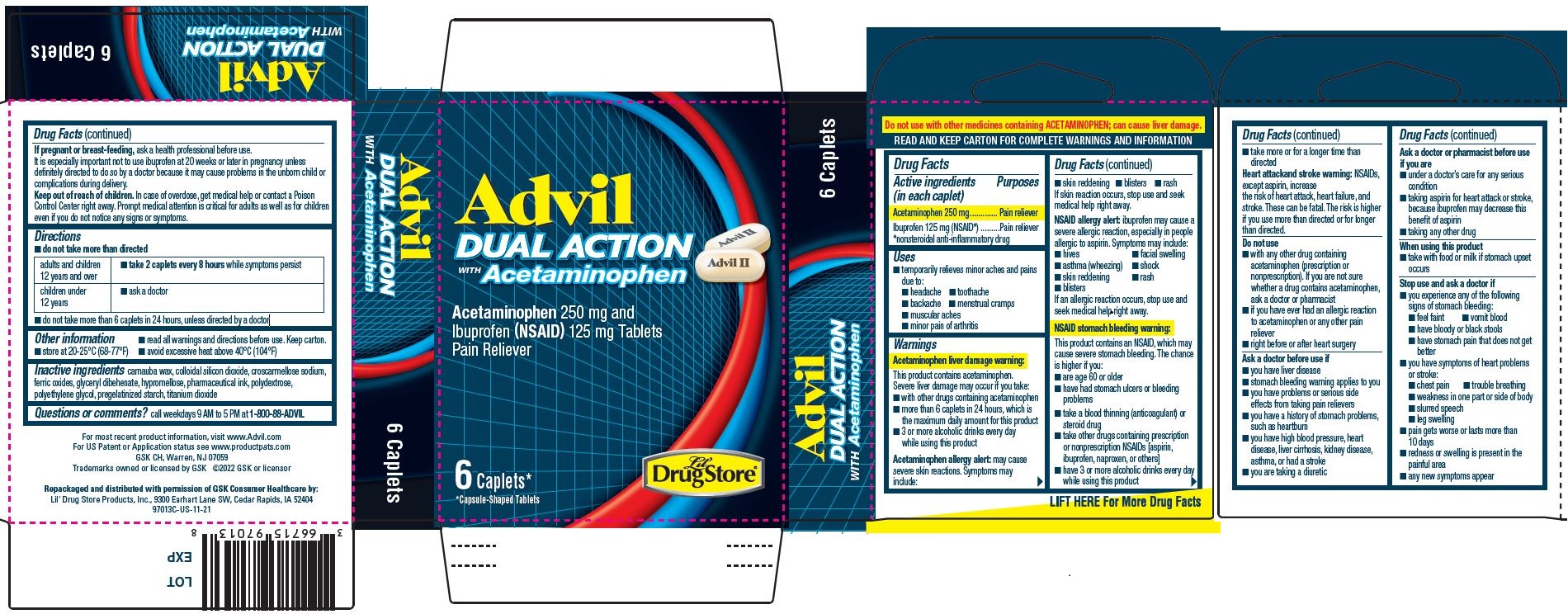 DRUG LABEL: Advil Dual Action with Acetaminophen
NDC: 66715-9601 | Form: TABLET, FILM COATED
Manufacturer: Lil' Drug Store Products, Inc.
Category: otc | Type: HUMAN OTC DRUG LABEL
Date: 20251201

ACTIVE INGREDIENTS: IBUPROFEN 125 mg/1 1; ACETAMINOPHEN 250 mg/1 1
INACTIVE INGREDIENTS: FERRIC OXIDE RED; HYPROMELLOSE, UNSPECIFIED; POLYETHYLENE GLYCOL, UNSPECIFIED; TITANIUM DIOXIDE; POLYDEXTROSE; CARNAUBA WAX; GLYCERYL DIBEHENATE; SILICON DIOXIDE; CROSCARMELLOSE SODIUM; STARCH, CORN

Advil Dual Action with Acetaminophen

Drug Facts

Active ingredients

Acetaminophen 250 mg

Ibuprofen 125 mg (NSAID*)

*nonsteroidal anti-inflammatory drug

Purposes

Pain reliever

Pain reliever

Uses

- temporarily relieves minor aches and pains due to:
- headache
- toothache
- backache
- menstrual cramps
- muscular aches
- minor pain of arthritis

Warnings

Acetaminophen liver damage warning

This product contains acetaminophen.
Severe liver damage may occur if you take:

- with other drugs containing acetaminophen
- more than 6 caplets in 24 hours, which is the maximum daily amount for this product
- 3 or more alcoholic drinks every day while using this product

Acetaminophen allergy alert: may cause severe skin reactions. Symptoms may include:

- skin reddening
- blisters
- rash

If skin reaction occurs, stop use and seek medical help right away.

NSAID allergy alert: ibuprofen may cause a severe allergic reaction, especially in people allergic to aspirin. Symptoms may include:

- hives
- facial swelling
- asthma (wheezing)
- shock
- skin reddening
- rash
- blisters

If an allergic reaction occurs, stop use and seek medical help right away.

NSAID stomach bleeding warning: This product contains an NSAID, which may cause severe stomach bleeding. The chance is higher if you:

- are age 60 or older
- have had stomach ulcers or bleeding problems
- take a blood thinning (anticoagulant) or steroid drug
- take other drugs containing prescription or nonprescription NSAIDs [aspirin, ibuprofen, naproxen, or others]
- have 3 or more alcoholic drinks every day while using this product
- take more or for a longer time than directed

Heart attackand stroke warning: NSAIDs, except aspirin, increase the risk of heart attack, heart failure, and stroke. These can be fatal. The risk is higher if you use more than directed or for longer than directed.

Do not use

- with any other drug containing acetaminophen (prescription or nonprescription). If you are not sure whether a drug contains acetaminophen, ask a doctor or pharmacist
- if you have ever had an allergic reaction to acetaminophen or any other pain reliever
- right before or after heart surgery

Ask a doctor before use if

- you have liver disease
- stomach bleeding warning applies to you
- you have problems or serious side effects from taking pain relievers
- you have a history of stomach problems, such as heartburn
- you have high blood pressure, heart disease, liver cirrhosis, kidney disease, asthma, or had a stroke
- you are taking a diuretic

Ask a doctor or pharmacist before use if you are

- under a doctor’s care for any serious condition
- taking aspirin for heart attack or stroke, because ibuprofen may decrease this benefit of aspirin
- taking any other drug

When using this product

- take with food or milk if stomach upset occurs

Stop use and ask a doctor if

- you experience any of the following signs of stomach bleeding:
- feel faint
- vomit blood
- have bloody or black stools
- have stomach pain that does not get better
- you have symptoms of heart problems or stroke:
- chest pain
- trouble breathing
- weakness in one part or side of body
- slurred speech
- leg swelling
- pain gets worse or lasts more than 10 days
- redness or swelling is present in the painful area
- any new symptoms appear

If pregnant or breast-feeding, ask a health professional before use. It is especially important not to use ibuprofen at 20 weeks or later in pregnancy unless definitely directed to do so by a doctor because it may cause problems in the unborn child or complications during delivery.

Keep out of reach of children. In case of overdose, get medical help or contact a Poison Control Center right away. Prompt medical attention is critical for adults as well as for children even if you do not notice any signs or symptoms.

Directions

- Do not take more than directed

adults and children 12 years and over | - take 2 caplets every 8 hours while symptoms persist
children under 12 years | - ask a doctor

- do not take more than 6 caplets in 24 hours, unless directed by a doctor

Other information

- read all warnings and directions before use. Keep carton.
- store at 20-25°C (68-77°F)
- avoid excessive heat above 40°C (104°F)

Inactive ingredients

carnauba wax, colloidal silicon dioxide, croscarmellose sodium, ferric oxides, glyceryl dibehenate, hypromellose, pharmaceutical ink, polydextrose, polyethylene glycol, pregelatinized starch, titanium dioxide

Questions or comments? call weekdays 9 AM to 5 PM at 1-800-88-ADVIL

Advil Dual Action with Acetaminophen, Lil' Drug Store

Advil

Dual Action

with Acetaminophen

[caplet image]

Acetaminophen 250 mg and
Ibuprofen (NSAID) 125 mg Tablets
Pain Reliever

6 Caplets*

*Capsule-Shaped Tablets

[Lil' Drug Store logo]

Advil Dual Action with Acetaminophen, Travel BASIX

Advil

Dual Action

with Acetaminophen

[caplet image]

Acetaminophen 250 mg and
Ibuprofen (NSAID) 125 mg Tablets
Pain Reliever

4 Caplets*

*Capsule-Shaped Tablets

[Travel BASIX logo]